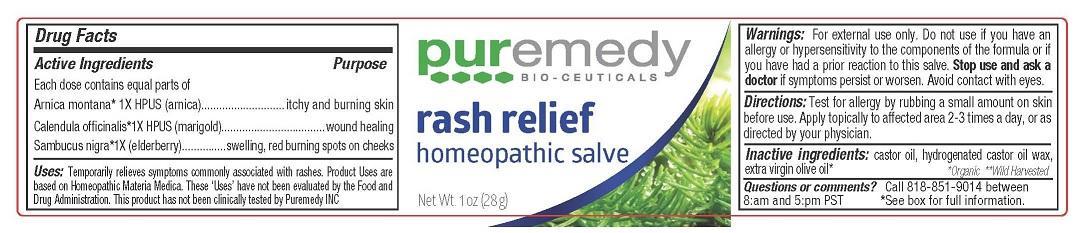 DRUG LABEL: RASH RELIEF
NDC: 52810-218 | Form: SALVE
Manufacturer: PUREMEDY
Category: homeopathic | Type: HUMAN OTC DRUG LABEL
Date: 20240111

ACTIVE INGREDIENTS: CALENDULA OFFICINALIS FLOWER 1 [hp_X]/100 mL; SAMBUCUS NIGRA FLOWER 1 [hp_X]/100 mL; ARNICA MONTANA 1 [hp_X]/100 mL
INACTIVE INGREDIENTS: OLIVE OIL; CASTOR OIL; HYDROGENATED CASTOR OIL

RASH RELIEF (52810-218)

ACTIVE INGREDIENTS

EACH DOSE CONTAINS EQUAL PARTS OF

ARNICA MONTANA 1X HPUS (ARNIC)

cALENDULA OFFICINALIS 1X HPUS (MARIGOLD)

SAMBUCUS NIGRA 1 X (ELDERBERRY)

PURPOSE

ITCHY AND BURNING SKIN

WOUND HEALING

SWELLING, RED BURING SPOTS ON CHEEKS

USES

TEMPORARILY RELIEVES SYMPTOMS COMMONLY ASSOCUATED WITH RASHES. PRODUCT USES ARE BASED ON HOMEOPATHIS MATERIA MEDICA. THESE 'USES' HAVE NOT BEEN EVALUATED BY THE FOOD AND DRUG ADMINISTRATION. THIS PRODUCT HAS NOT BEEN CLINICALLY TESTED BY PUREMEDY INC.

DIRECTIONS

TEST FOR ALLERGY BY RUBBING a small amount on skin before use. apply topically to affected area 2-3 times a day, or as directed by your physician.

INACTIVE INGREDIENTS

CASTOR OIL, HYDROGENATED CASTOR OIL WAX, EXTRA VIRGIN OLIVE OIL

WARNINGS

FOR EXTERNAL USE ONLY. DO NOT USE IF YOU HAVE AN ALLERGY OR HYPERSENSITIVITY TO THE COMPONENTS OF THE FORMULA OR IF YOU HAVE HAD A PRIOR REACTION TO THIS SALVE. STOP USE AND ASK A DOCTOR IF SYMPTOMS PERSISTS OR WORSEN. AVOID CONTACT WITH EYES.

KEEP ALL DRUGS OUT OF REACH OF CHILDREN.

QUESTIONS OR COMMENTS?

CALL 818-851-9014 BETWEEN 8:AM AND 5:PM PST